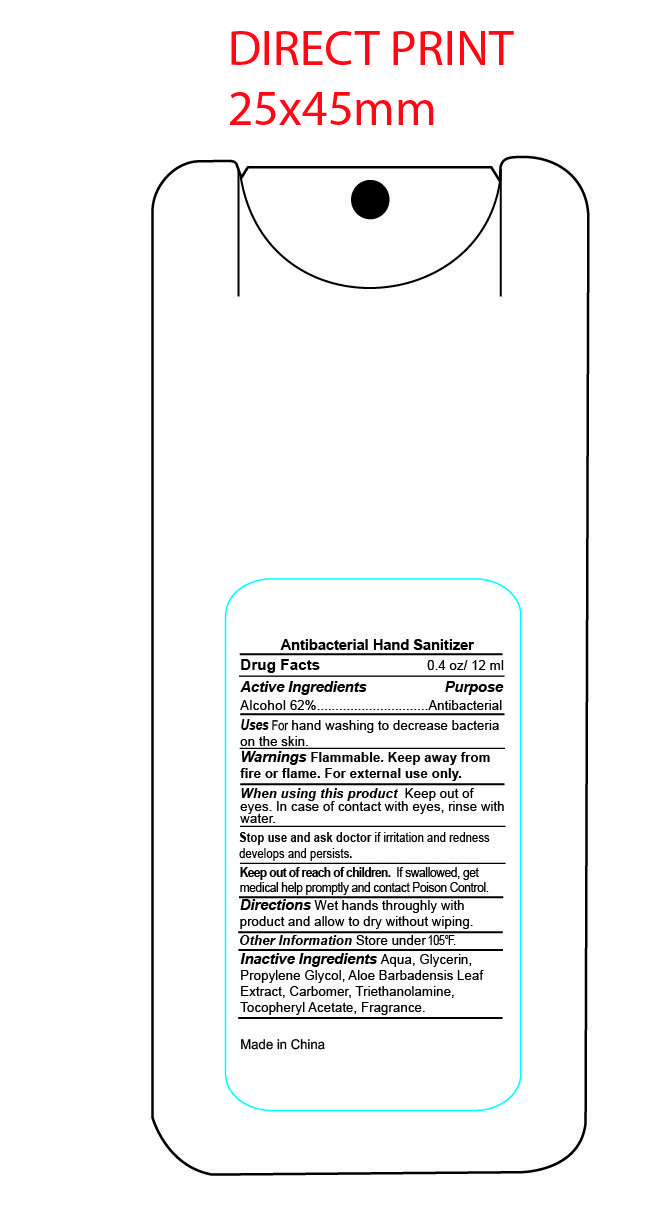 DRUG LABEL: antiseptic hand sanitizer
NDC: 82953-007 | Form: LIQUID
Manufacturer: Cosmuses Cosmetics (Ningbo) Co., Ltd.
Category: otc | Type: HUMAN OTC DRUG LABEL
Date: 20231211

ACTIVE INGREDIENTS: ALCOHOL 62 mL/100 mL
INACTIVE INGREDIENTS: .ALPHA.-TOCOPHEROL ACETATE; GLYCERIN; PROPYLENE GLYCOL; ALOE VERA LEAF; WATER; CARBOMER 940; TROLAMINE

antiseptic hand sanitizer

Active Ingredients

Alcohol 62%

Purpose

Antibacterial

Uses

For hand washing to decrease bacteria on the skin.

Warnings

Flammable. Keep away from fire or flame. For external use only.

When using this product, keep out of eyes. In case of contact with eyes, rinse with water.

Stop use and ask doctor if irritation and redness develops and persists.

Keep out of reach of children. If swallowed, get medical help promptly and contact Poison Control.

Directions

Wet hands throughly with product and allow to dry without wiping.

Other information Store under 105oF.

Inactive Ingredients

Aqua, Glycerin, Propylene Glycol, Aloe Barbadensis Leaf Extract, Carbomer, Triethanolamine, Tocopheryl Acetate, Fragrance.